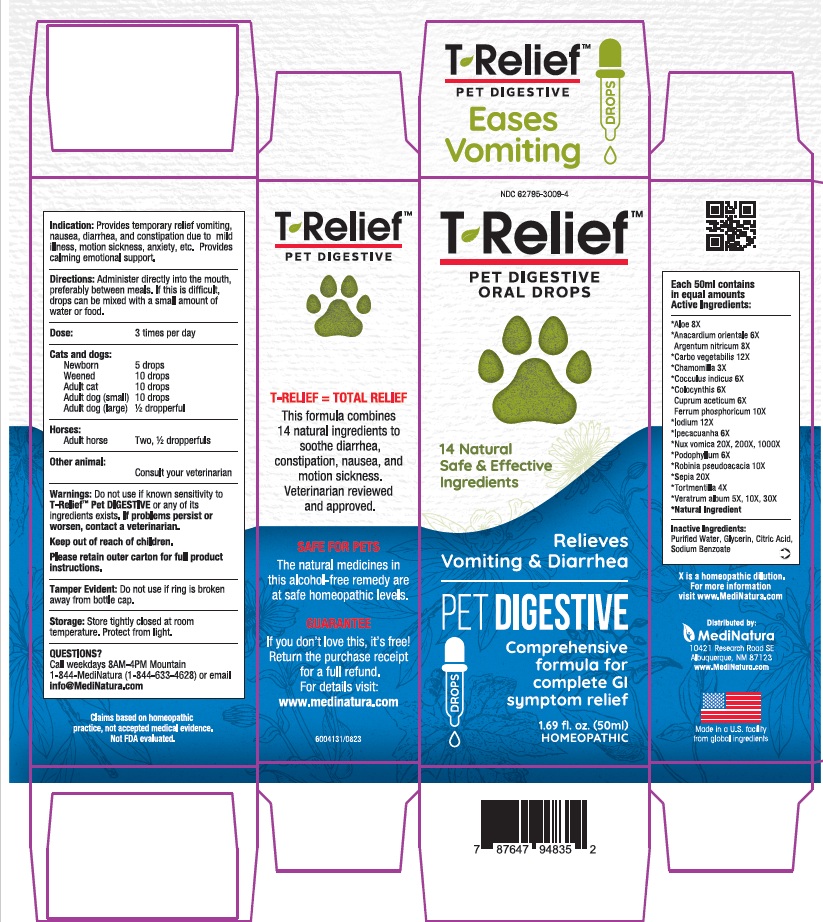 DRUG LABEL: T Relief Pet Digestive
NDC: 62795-3009 | Form: SOLUTION/ DROPS
Manufacturer: MediNatura New Mexico Inc
Category: homeopathic | Type: OTC ANIMAL DRUG LABEL
Date: 20251228

ACTIVE INGREDIENTS: ALOE 8 [hp_X]/50 mL; SEMECARPUS ANACARDIUM JUICE 6 [hp_X]/50 mL; SILVER NITRATE 8 [hp_X]/50 mL; ACTIVATED CHARCOAL 12 [hp_X]/50 mL; MATRICARIA CHAMOMILLA WHOLE 3 [hp_X]/50 mL; ANAMIRTA COCCULUS WHOLE 6 [hp_X]/50 mL; CITRULLUS COLOCYNTHIS FRUIT PULP 6 [hp_X]/50 mL; CUPRIC ACETATE 6 [hp_X]/50 mL; FERROSOFERRIC PHOSPHATE 10 [hp_X]/50 mL; IODINE 12 [hp_X]/50 mL; IPECAC 6 [hp_X]/50 mL; STRYCHNOS NUX-VOMICA SEED 20 [hp_X]/50 mL; PODOPHYLLUM RESIN 6 [hp_X]/50 mL; ROBINIA PSEUDOACACIA BARK 10 [hp_X]/50 mL; SEPIA OFFICINALIS JUICE 20 [hp_X]/50 mL; POTENTILLA ERECTA ROOT 4 [hp_X]/50 mL; VERATRUM ALBUM ROOT 5 [hp_X]/50 mL
INACTIVE INGREDIENTS: WATER; GLYCERIN; CITRIC ACID ACETATE; Sodium Benzoate

T Relief Pet Digestive

Warnings:

Do not use if known sensitivity to
T-Relief™ Pet DIGESTIVE or any of its
ingredients exists. If problems persist or
worsen, contact a veterinarian.
Keep out of reach of children.
Please retain outer carton for full product
instructions.

Indication:

Provides temporary relief vomiting,
nausea, diarrhea, and constipation due to mild
illness, motion sickness, anxiety, etc. Provides
calming emotional support.

Directions

: Administer directly into the mouth,
preferably between meals. If this is difficult,
drops can be mixed with a small amount of
water or food.
Dose: 3 times per day
Cats and dogs:
Newborn 5 drops
Weened 10 drops
Adult cat 10 drops
Adult dog (small) 10 drops
Adult dog (large) ½ dropperful
Horses:
Adult horse Two, ½ dropperfuls
Other animal:
Consult your veterinarian

inactive Ingredients:

Purified Water, Glycerin, Citric Acid,
Sodium Benzoate

Keep out of reach of children.

Active Ingredients

Each 50ml contains
in equal amounts
Active Ingredients:
*Aloe 8X
*Anacardium orientale 6X
Argentum nitricum 8X
*Carbo vegetabilis 12X
*Chamomilla 3X
*Cocculus indicus 6X
*Colocynthis 6X
Cuprum aceticum 6X
Ferrum phosphoricum 10X
*Iodium 12X
*Ipecacuanha 6X
*Nux vomica 20X, 200X, 1000X
*Podophyllum 6X
*Robinia pseudoacacia 10X
*Sepia 20X
*Tortmentilla 4X
*Veratrum album 5X, 10X, 30X
*Natural Ingredient

Purpose

Relieves
Vomiting & Diarrhea